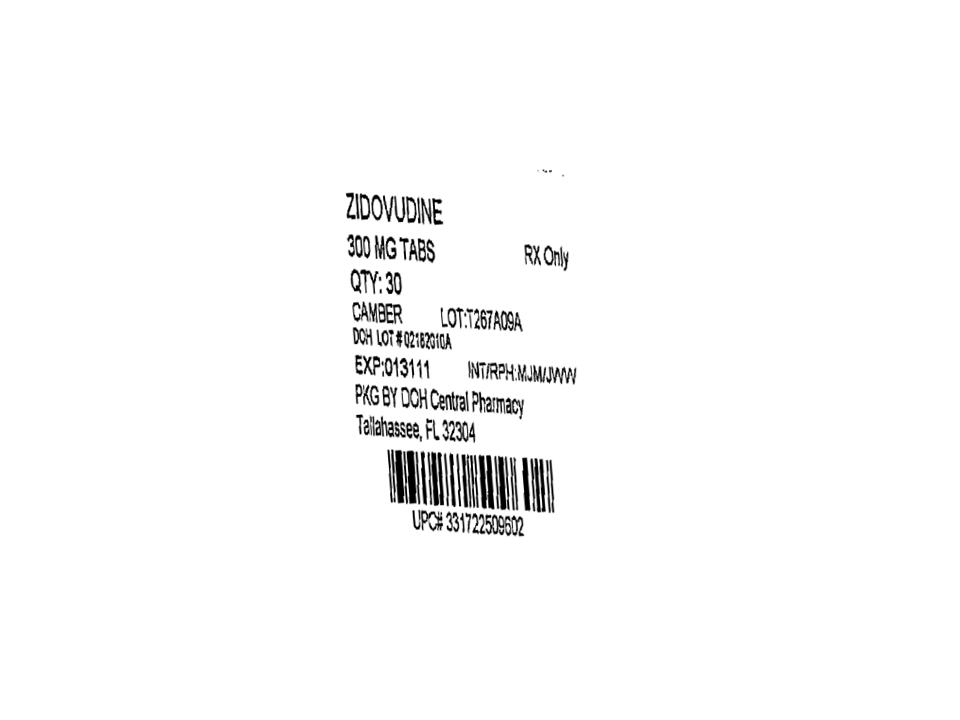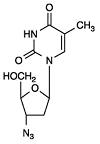 DRUG LABEL: Zidovudine
NDC: 53808-0812 | Form: TABLET, FILM COATED
Manufacturer: DOH CENTRAL PHARMACY
Category: prescription | Type: HUMAN PRESCRIPTION DRUG LABEL
Date: 20170120

ACTIVE INGREDIENTS: ZIDOVUDINE 300 mg/1 1
INACTIVE INGREDIENTS: HYPROMELLOSES; MAGNESIUM STEARATE; CELLULOSE, MICROCRYSTALLINE; POLYETHYLENE GLYCOL; SODIUM STARCH GLYCOLATE TYPE A POTATO; TITANIUM DIOXIDE

HIGHLIGHTS OF PRESCRIBING INFORMATION

These highlights do not include all the information needed to use ZIDOVUDINE . See full prescribing information for ZIDOVUDINE. Initial U.S. Approval 1987

RECENT MAJOR CHANGES

Dosage and Administration, Pediatric Patients (2.1) September 2008

WARNING: RISK OF HEMATOLOGICAL TOXICITY, MYOPATHY, LACTIC ACIDOSIS

See full prescribing information for complete boxed warning.

- Hematologic toxicity including neutropenia and severe anemia have been associated with the use of zidovudine. (5.1)
- Symptomatic myopathy associated with prolonged use of zidovudine. (5.2)
- Lactic acidosis and severe hepatomegaly with steatosis, including fatal cases, have been reported with the use of nucleoside analogues including zidovudine. Suspend treatment if clinical or laboratory findings suggestive of lactic acidosis or pronounced hepatotoxicity occur. (5.3)

INDICATIONS AND USAGE

Zidovudine tablets are a nucleoside analogue reverse transcriptase inhibitor indicated for:

- Treatment of Human Immunodeficiency Virus (HIV-1) infection in combination with other antiretroviral agents. (1.1)
- Prevention of maternal-fetal HIV-1 transmission. (1.2)

DOSAGE AND ADMINISTRATION

- Treatment of HIV-1 infection:

Adults: 600 mg/day in divided doses with other antiretroviral agents.
Pediatric patients (6 weeks to <18 years of age): Dosage should be calculated based on body weight not to exceed adult dose. (2.1)

- Prevention of maternal-fetal HIV-1 transmission:

Specific dosage instructions for mother and infant. (2.2)

- Patients with severe anemia and/or neutropenia:

Dosage interruption may be necessary. (2.3)

- Renal Impairment – Recommended dosage in hemodialysis or peritoneal dialysis patients is 100 mg every 6 to 8 hours. (2.4)

3 DOSAGE FORMS AND STRENGTHS

Tablets: 300 mg (3)

4 CONTRAINDICATIONS

Hypersensitivity to zidovudine (e.g., anaphylaxis, Stevens-Johnson syndrome). (4)

WARNINGS AND PRECAUTIONS

- Hematologic toxicity/bone marrow suppression including neutropenia and severe anemia have been associated with the use of zidovudine. (5.1)
- Symptomatic myopathy associated with prolonged use of zidovudine. (5.2)
- Lactic acidosis and severe hepatomegaly with steatosis, including fatal cases, have been reported with the use of nucleoside analogues including zidovudine. Suspend treatment if clinical or laboratory findings suggestive of lactic acidosis or pronounced hepatotoxicity occur. (5.3)
- Exacerbation of anemia has been reported in HIV-1/HCV co-infected patients receiving ribavirin and zidovudine. Coadministration of ribavirin and zidovudine is not advised. (5.4)
- Hepatic decompensation, (some fatal), has occurred in HIV-1/HCV co-infected patients receiving combination antiretroviral therapy and interferon alfa with/without ribavirin. Discontinue zidovudine as medically appropriate and consider dose reduction or discontinuation of interferon alfa, ribavirin, or both. (5.4)
- Zidovudine should not be administered with other zidovudine-containing combination products. (5.5)
- Immune reconstitution syndrome (5.6) and redistribution/accumulation of body fat (5.7) have been reported in patients treated with combination antiretroviral therapy.

ADVERSE REACTIONS

- The most commonly reported adverse reactions (incidence ≥15%) in adult HIV-1 clinical studies were headache, malaise, nausea, anorexia, and vomiting. (6.1)
- The most commonly reported adverse reactions (incidence ≥15%) in pediatric HIV-1 clinical studies were fever, cough, and digestive disorders. (6.1)
- The most commonly reported adverse reactions in neonates (incidence ≥15%) in the prevention of maternal-fetal transmission of HIV-1 clinical trial were anemia and neutropenia. (6.1)

To report SUSPECTED ADVERSE REACTIONS, contact FDA at 1-800-FDA-1088 or www.fda.gov/medwatch.

DRUG INTERACTIONS

- Stavudine: Concomitant use with zidovudine should be avoided. (7.1)
- Doxorubicin: Use with zidovudine should be avoided. (7.2)
- Bone marrow suppressive/cytotoxic agents: May increase the hematologic toxicity of zidovudine. (7.3)

USE IN SPECIFIC POPULATIONS

Pregnancy: Physicians are encouraged to register patients in the Antiretroviral Pregnancy Registry by calling 1-800-258-4263. (8.1)

FULL PRESCRIBING INFORMATION

WARNING: RISK OF HEMATOLOGICAL TOXICITY, MYOPATHY, LACTIC ACIDOSIS

Zidovudine has been associated with hematologic toxicity including neutropenia and severe anemia, particularly in patients with advanced HIV-1 disease [see Warnings and Precautions (5.1)].
Prolonged use of zidovudine has been associated with symptomatic myopathy [see Warnings and Precautions (5.2)].
Lactic acidosis and severe hepatomegaly with steatosis, including fatal cases, have been reported with the use of nucleoside analogues alone or in combination, including zidovudine and other antiretrovirals. Suspend treatment if clinical or laboratory findings suggestive of lactic acidosis or pronounced hepatotoxicity occur [see Warnings and Precautions (5.3)].

INDICATIONS AND USAGE

1.1 Treatment of HIV-1

Zidovudine tablets, a nucleoside reverse transcriptase inhibitor, are indicated in combination with other antiretroviral agents for the treatment of HIV-1 infection.

1.2 Prevention of Maternal-Fetal HIV-1 Transmission

Zidovudine tablets are indicated for the prevention of maternal-fetal HIV-1 transmission [see Dosage and Administration (2.2)]. The indication is based on a dosing regimen that included 3 components:

1. antepartum therapy of HIV-1 infected mothers
2. intrapartum therapy of HIV-1 infected mothers
3. post-partum therapy of HIV-1 exposed neonate.

Points to consider prior to initiating zidovudine tablets in pregnant women for the prevention of maternal-fetal HIV-1 transmission include:

- In most cases, zidovudine tablets for prevention of maternal-fetal HIV-1 transmission should be given in combination with other antiretroviral drugs.
- Prevention of HIV-1 transmission in women who have received zidovudine tablets for a prolonged period before pregnancy has not been evaluated.
- Because the fetus is most susceptible to the potential teratogenic effects of drugs during the first 10 weeks of gestation and the risks of therapy with zidovudine tablets during that period are not fully known, women in the first trimester of pregnancy who do not require immediate initiation of antiretroviral therapy for their own health may consider delaying use; this indication is based on use after 14 weeks gestation.

DOSAGE AND ADMINISTRATION

2.1 Treatment of HIV-1 Infection

Adults: The recommended oral dose of zidovudine tablets is 600 mg/day in divided doses in combination with other antiretroviral agents.
Pediatric Patients (6 weeks to <18 years of age): Healthcare professionals should pay special attention to accurate calculation of the dose of zidovudine tablets, transcription of the medication order, dispensing information, and dosing instructions to minimize risk for medication dosing errors.
Prescribers should calculate the appropriate dose of zidovudine tablets for each child based on body weight (kg) and should not exceed the recommended adult dose.
Before prescribing zidovudine tablets, children should be assessed for the ability to swallow tablets. If a child is unable to reliably swallow a zidovudine tablet, the zidovudine syrup formulation should be prescribed.
The recommended dosage in pediatric patients 6 weeks of age and older and weighing ≥4 kg is provided in Table 1. Zidovudine syrup should be used to provide accurate dosage when whole tablets are not appropriate.

Table 1: Recommended Pediatric Dosage of Zidovudine Tablets
Body Weight (kg) | Total Daily Dose | Dosage Regimen and Dose
Body Weight (kg) | Total Daily Dose | b.i.d. | t.i.d.
4 to <9 | 24 mg/kg/day | 12 mg/kg | 8 mg/kg
≥9 to <30 | 18 mg/kg/day | 9 mg/kg | 6 mg/kg
≥30 | 600 mg/day | 300 mg | 200 mg

Alternatively, dosing for zidovudine tablets can be based on body surface area (BSA) for each child. The recommended oral dose of zidovudine tablets is 480 mg/m^2/day in divided doses (240 mg/m^2 twice daily or 160 mg/m^2 three times daily). In some cases the dose calculated by mg/kg will not be the same as that calculated by BSA.

2.2 Prevention of Maternal-Fetal HIV-1 Transmission

The recommended dosage regimen for administration to pregnant women (>14 weeks of pregnancy) and their neonates is:
Maternal Dosing: 100 mg orally 5 times per day until the start of labor [see Clinical Studies (14.3)]. During labor and delivery, intravenous zidovudine should be administered at 2 mg/kg (total body weight) over 1 hour followed by a continuous intravenous infusion of 1 mg/kg/hour (total body weight) until clamping of the umbilical cord.
Neonatal Dosing: 2 mg/kg orally every 6 hours starting within 12 hours after birth and continuing through 6 weeks of age. Neonates unable to receive oral dosing may be administered zidovudine intravenously at 1.5 mg/kg, infused over 30 minutes, every 6 hours.

2.3 Patients With Severe Anemia and/or Neutropenia

Significant anemia (hemoglobin <7.5 g/dL or reduction >25% of baseline) and/or significant neutropenia (granulocyte count <750 cells/mm^3 or reduction >50% from baseline) may require a dose interruption until evidence of marrow recovery is observed [see Warnings and Precautions (5.1)]. In patients who develop significant anemia, dose interruption does not necessarily eliminate the need for transfusion. If marrow recovery occurs following dose interruption, resumption in dose may be appropriate using adjunctive measures such as epoetin alfa at recommended doses, depending on hematologic indices such as serum erythropoetin level and patient tolerance.

2.4 Patients With Renal Impairment

End-Stage Renal Disease: In patients maintained on hemodialysis or peritoneal dialysis, the recommended dosage is 100 mg every 6 to 8 hours [see Clinical Pharmacology (12.3)].

2.5 Patients With Hepatic Impairment

There are insufficient data to recommend dose adjustment of zidovudine tablets in patients with mild to moderate impaired hepatic function or liver cirrhosis.

3 DOSAGE FORMS AND STRENGTHS

Zidovudine Tablets USP, 300 mg are white colored, biconvex, round, film-coated tablets debossed with ‘D’ on one side and ‘11’ on other side.

4 CONTRAINDICATIONS

Zidovudine tablets are contraindicated in patients who have had potentially life-threatening allergic reactions (e.g., anaphylaxis, Stevens-Johnson syndrome) to any of the components of the formulations.

WARNINGS AND PRECAUTIONS

5.1 Hematologic Toxicity/Bone Marrow Suppression

Zidovudine should be used with caution in patients who have bone marrow compromise evidenced by granulocyte count <1,000 cells/mm^3 or hemoglobin <9.5 g/dL. Hematologic toxicities appear to be related to pretreatment bone marrow reserve and to dose and duration of therapy. In patients with advanced symptomatic HIV-1 disease, anemia and neutropenia were the most significant adverse events observed. In patients who experience hematologic toxicity, a reduction in hemoglobin may occur as early as 2 to 4 weeks, and neutropenia usually occurs after 6 to 8 weeks. There have been reports of pancytopenia associated with the use of zidovudine, which was reversible in most instances after discontinuance of the drug. However, significant anemia, in many cases requiring dose adjustment, discontinuation of zidovudine, and/or blood transfusions, has occurred during treatment with zidovudine alone or in combination with other antiretrovirals.
Frequent blood counts are strongly recommended to detect severe anemia or neutropenia in patients with poor bone marrow reserve, particularly in patients with advanced HIV-1 disease who are treated with zidovudine. For HIV-1-infected individuals and patients with asymptomatic or early HIV-1 disease, periodic blood counts are recommended. If anemia or neutropenia develops, dosage interruption may be needed [see Dosage and Administration (2.3)].

5.2 Myopathy

Myopathy and myositis with pathological changes, similar to that produced by HIV-1 disease, have been associated with prolonged use of zidovudine.

5.3 Lactic Acidosis/Severe Hepatomegaly With Steatosis

Lactic acidosis and severe hepatomegaly with steatosis, including fatal cases, have been reported with the use of nucleoside analogues alone or in combination, including zidovudine and other antiretrovirals. A majority of these cases have been in women. Obesity and prolonged exposure to antiretroviral nucleoside analogues may be risk factors. Particular caution should be exercised when administering zidovudine to any patient with known risk factors for liver disease; however, cases have also been reported in patients with no known risk factors. Treatment with zidovudine should be suspended in any patient who develops clinical or laboratory findings suggestive of lactic acidosis or pronounced hepatotoxicity (which may include hepatomegaly and steatosis even in the absence of marked transaminase elevations).

5.4 Use With Interferon- and Ribavirin-Based Regimens in HIV-1/HCV Co-Infected Patients

In vitro studies have shown ribavirin can reduce the phosphorylation of pyrimidine nucleoside analogues such as zidovudine. Although no evidence of a pharmacokinetic or pharmacodynamic interaction (e.g., loss of HIV-1/HCV virologic suppression) was seen when ribavirin was coadministered with zidovudine in HIV-1/HCV co-infected patients [see Clinical Pharmacology (12.3)], exacerbation of anemia due to ribavirin has been reported when zidovudine is part of the HIV regimen. Coadministration of ribavirin and zidovudine is not advised. Consideration should be given to replacing zidovudine in established combination HIV-1/HCV therapy, especially in patients with a known history of zidovudine-induced anemia.
Hepatic decompensation (some fatal) has occurred in HIV-1/HCV co-infected patients receiving combination antiretroviral therapy for HIV-1 and interferon alfa with or without ribavirin. Patients receiving interferon alfa with or without ribavirin and zidovudine should be closely monitored for treatment-associated toxicities, especially hepatic decompensation, neutropenia, and anemia.
Discontinuation of zidovudine should be considered as medically appropriate. Dose reduction or discontinuation of interferon alfa, ribavirin, or both should also be considered if worsening clinical toxicities are observed, including hepatic decompensation (e.g., Childs Pugh >6) (see the complete prescribing information for interferon and ribavirin).

5.5 Use With Other Zidovudine-Containing Products

Zidovudine should not be administered with combination products that contain zidovudine as one of their components (e.g., COMBIVIR® or TRIZIVIR®).

5.6 Immune Reconstitution Syndrome

Immune reconstitution syndrome has been reported in patients treated with combination antiretroviral therapy, including zidovudine. During the initial phase of combination antiretroviral treatment, patients whose immune systems respond may develop an inflammatory response to indolent or residual opportunistic infections (such as Mycobacterium avium infection, cytomegalovirus, Pneumocystis jirovecii pneumonia [PCP], or tuberculosis), which may necessitate further evaluation and treatment.

5.7 Fat Redistribution

Redistribution/accumulation of body fat, including central obesity, dorsocervical fat enlargement (buffalo hump), peripheral wasting, facial wasting, breast enlargement, and “cushingoid appearance,” have been observed in patients receiving antiretroviral therapy. The mechanism and long-term consequences of these events are currently unknown. A causal relationship has not been established.

ADVERSE REACTIONS

6.1 Clinical Trials Experience

The following adverse reactions are discussed in greater detail in other sections of the labeling:

- Hematologic toxicity, including neutropenia and anemia [see Boxed Warning, Warnings and Precautions (5.1)].
- Symptomatic myopathy [see Boxed Warning, Warnings and Precautions (5.2)].
- Lactic acidosis and severe hepatomegaly with steatosis [see Boxed Warning, Warnings and Precautions (5.3)].
- Hepatic decompensation in patients co-infected with HIV-1 and hepatitis C [see Warnings and Precautions (5.4)].

Because clinical trials are conducted under widely varying conditions, adverse reaction rates observed in the clinical trials of a drug cannot be directly compared to rates in the clinical trials of another drug and may not reflect the rates observed in practice.

Adults: The frequency and severity of adverse reactions associated with the use of zidovudine are greater in patients with more advanced infection at the time of initiation of therapy.
Table 2 summarizes events reported at a statistically significant greater incidence for patients receiving zidovudine in a monotherapy study.

Table 2. Percentage (%) of Patients With Adverse Reactions* in Asymptomatic HIV-1 Infection (ACTG 019)
Adverse Reaction | Zidovudine 500 mg/day (n = 453) | Placebo (n = 428)
Body as a whole Asthenia Headache Malaise | 9%† 63% 53% | 6% 53% 45%
Gastrointestinal Anorexia Constipation Nausea Vomiting | 20% 6%† 51% 17% | 11% 4% 30% 10%
* Reported in ≥5% of study population.
† Not statistically significant versus placebo.

In addition to the adverse reactions listed in Table 2, adverse reactions observed at an incidence of ≥5% in any treatment arm in clinical studies (NUCA3001, NUCA3002, NUCB3001, and NUCB3002) were abdominal cramps, abdominal pain, arthralgia, chills, dyspepsia, fatigue, insomnia, musculoskeletal pain, myalgia, and neuropathy. Additionally, in these studies hyperbilirubinemia was reported at an incidence of ≤0.8%.
Selected laboratory abnormalities observed during a clinical study of monotherapy with zidovudine are shown in Table 3.

Table 3. Frequencies of Selected (Grade 3/4) Laboratory Abnormalities in Patients With Asymptomatic HIV-1 Infection (ACTG 019)
Test (Abnormal Level) | Zidovudine 500 mg/day (n = 453) | Placebo (n = 428)
Anemia (Hgb<8 g/dL) Granulocytopenia (<750 cells/mm^3) Thrombocytopenia (platelets<50,000/mm^3) ALT (>5 x ULN) AST (>5 x ULN) | 1% 2% 0% 3% 1% | <1% 2% <1% 3% 2%
ULN = Upper limit of normal.

Pediatrics: The clinical adverse reactions reported among adult recipients of zidovudine may also occur in pediatric patients.
Study ACTG300: Selected clinical adverse reactions and physical findings with a ≥5% frequency during therapy with EPIVIR 4 mg/kg twice daily plus zidovudine 160 mg/m^2 3 times daily compared with didanosine in therapy-naive (≤56 days of antiretroviral therapy) pediatric patients are listed in Table 4.

Table 4. Selected Clinical Adverse Reactions and Physical Findings (≥5% Frequency) in Pediatric Patients in Study ACTG300
Adverse Reaction | EPIVIR plus Zidovudine (n = 236) | Didanosine (n = 235)
Body as a whole Fever | 25% | 32%
Digestive Hepatomegaly Nausea & vomiting Diarrhea Stomatitis Splenomegaly | 11% 8% 8% 6% 5% | 11% 7% 6% 12% 8%
Respiratory Cough Abnormal breath sounds/wheezing | 15% 7% | 18% 9%
Ear, Nose, and Throat Signs or symptoms of ears* Nasal discharge or congestion | 7% 8% | 6% 11%
Other Skin rashes Lymphadenopathy | 12% 9% | 14% 11%
*Includes pain, discharge, erythema, or swelling of an ear.

Selected laboratory abnormalities experienced by therapy-naive (≤56 days of antiretroviral therapy) pediatric patients are listed in Table 5.

Table 5. Frequencies of Selected (Grade 3/4) Laboratory Abnormalities in Pediatric Patients in Study ACTG300
Test (Abnormal Level) | EPIVIR plus Zidovudine | Didanosine
Neutropenia (ANC<400 cells/mm^3) Anemia (Hgb<7 g/dL) Thrombocytopenia (platelets<50,000/mm^3) ALT (>10 x ULN) AST (>10 x ULN) Lipase (>2.5 x ULN) Total amylase (>2.5 x ULN) | 8% 4% 1% 1% 2% 3% 3% | 3% 2% 3% 3% 4% 3% 3%
ULN = Upper limit of normal.
ANC = Absolute neutrophil count.

Macrocytosis was reported in the majority of pediatric patients receiving zidovudine 180 mg/m^2 every 6 hours in open-label studies. Additionally, adverse reactions reported at an incidence of <6% in these studies were congestive heart failure, decreased reflexes, ECG abnormality, edema, hematuria, left ventricular dilation, nervousness/irritability, and weight loss.
Use for the Prevention of Maternal-Fetal Transmission of HIV-1: In a randomized, double-blind, placebo-controlled trial in HIV-1-infected women and their neonates conducted to determine the utility of zidovudinefor the prevention of maternal-fetal HIV-1 transmission, zidovudine syrup at 2 mg/kg was administered every 6 hours for 6 weeks to neonates beginning within 12 hours following birth. The most commonly reported adverse reactions were anemia (hemoglobin <9 g/dL) and neutropenia (<1,000 cells/mm^3). Anemia occurred in 22% of the neonates who received zidovudine and in 12% of the neonates who received placebo. The mean difference in hemoglobin values was less than 1 g/dL for neonates receiving zidovudine compared with neonates receiving placebo. No neonates with anemia required transfusion and all hemoglobin values spontaneously returned to normal within 6 weeks after completion of therapy with zidovudine. Neutropenia in neonates was reported with similar frequency in the group that received zidovudine (21%) and in the group that received placebo (27%). The long-term consequences of in utero and infant exposure to zidovudine are unknown.

6.2 Postmarketing Experience

In addition to adverse reactions reported from clinical trials, the following reactions have been identified during postmarketing use of zidovudine. Because they are reported voluntarily from a population of unknown size, estimates of frequency cannot be made. These reactions have been chosen for inclusion due to a combination of their seriousness, frequency of reporting, or potential causal connection to zidovudine.
Body as a Whole: Back pain, chest pain, flu-like syndrome, generalized pain, redistribution/accumulation of body fat [see Warnings and Precautions (5.6)].
Cardiovascular: Cardiomyopathy, syncope.
Endocrine: Gynecomastia.
Eye: Macular edema.
Gastrointestinal: Dysphagia, flatulence, oral mucosa pigmentation, mouth ulcer.
General: Sensitization reactions including anaphylaxis and angioedema, vasculitis.
Hemic and Lymphatic: Aplastic anemia, hemolytic anemia, leukopenia, lymphadenopathy, pancytopenia with marrow hypoplasia, pure red cell aplasia.
Hepatobiliary Tract and Pancreas: Hepatitis, hepatomegaly with steatosis, jaundice, lactic acidosis, pancreatitis.
Musculoskeletal: Increased CPK, increased LDH, muscle spasm, myopathy and myositis with pathological changes (similar to that produced by HIV-1 disease), rhabdomyolysis, tremor.
Nervous: Anxiety, confusion, depression, dizziness, loss of mental acuity, mania, paresthesia, seizures, somnolence, vertigo.
Respiratory: Dyspnea, rhinitis, sinusitis.
Skin: Changes in skin and nail pigmentation, pruritus, Stevens-Johnson syndrome, toxic epidermal necrolysis, sweat, urticaria.
Special Senses: Amblyopia, hearing loss, photophobia, taste perversion.
Urogenital: Urinary frequency, urinary hesitancy.

DRUG INTERACTIONS

7.1 Antiretroviral Agents

Stavudine: Concomitant use of zidovudine with stavudine should be avoided since an antagonistic relationship has been demonstrated in vitro.
Nucleoside Analogues Affecting DNA Replication: Some nucleoside analogues affecting DNA replication, such as ribavirin, antagonize the in vitro antiviral activity of zidovudine against HIV-1; concomitant use of such drugs should be avoided.

7.2 Doxorubicin

Concomitant use of zidovudine with doxorubicin should be avoided since an antagonistic relationship has been demonstrated in vitro.

7.3 Hematologic/Bone Marrow Suppressive/Cytotoxic Agents

Coadministration of ganciclovir, interferon alfa, ribavirin, and other bone marrow suppressive or cytotoxic agents may increase the hematologic toxicity of zidovudine.

USE IN SPECIFIC POPULATIONS

8.1 Pregnancy

Teratogenic Effects
Pregnancy Category C.
In humans, treatment with zidovudine during pregnancy reduced the rate of maternal-fetal HIV-1 transmission from 24.9% for infants born to placebo-treated mothers to 7.8% for infants born to mothers treated with zidovudine [see Clinical Studies (14.3)]. There were no differences in pregnancy-related adverse events between the treatment groups. Animal reproduction studies in rats and rabbits showed evidence of embryotoxicity and increased fetal malformations.
A randomized, double-blind, placebo-controlled trial was conducted in HIV-1-infected pregnant women to determine the utility of zidovudine for the prevention of maternal-fetal HIV-1-transmission [see Clinical Studies (14.3)]. Congenital abnormalities occurred with similar frequency between neonates born to mothers who received zidovudine and neonates born to mothers who received placebo. The observed abnormalities included problems in embryogenesis (prior to 14 weeks) or were recognized on ultrasound before or immediately after initiation of study drug.
Increased fetal resorptions occurred in pregnant rats and rabbits treated with doses of zidovudine that produced drug plasma concentrations 66 to 226 times (rats) and 12 to 87 times (rabbits) the mean steady-state peak human plasma concentration following a single 100 mg dose of zidovudine. There were no other reported developmental anomalies. In another developmental toxicity study, pregnant rats received zidovudine up to near-lethal doses that produced peak plasma concentrations 350 times peak human plasma concentrations (300 times the daily AUC in humans given 600 mg/day zidovudine). This dose was associated with marked maternal toxicity and an increased incidence of fetal malformations. However, there were no signs of teratogenicity at doses up to one fifth the lethal dose [see Nonclinical Toxicology (13.2)].
Antiretroviral Pregnancy Registry: To monitor maternal-fetal outcomes of pregnant women exposed to zidovudine, an Antiretroviral Pregnancy Registry has been established. Physicians are encouraged to register patients by calling 1-800-258-4263.

8.3 Nursing Mothers

Zidovudine is excreted in human milk [see Clinical Pharmacology (12.3)].
The Centers for Disease Control and Prevention recommend that HIV-1-infected mothers in the United States not breastfeed their infants to avoid risking postnatal transmission of HIV-1 infection. Because of both the potential for HIV-1 transmission and the potential for serious adverse reactions in nursing infants, mothers should be instructed not to breastfeed if they are receiving zidovudine.

8.4 Pediatric Use

Zidovudine has been studied in HIV-1-infected pediatric patients ≥6 weeks of age who had HIV-1-related symptoms or who were asymptomatic with abnormal laboratory values indicating significant HIV-1-related immunosuppression. Zidovudine has also been studied in neonates perinatally exposed to HIV-1 [see Dosage and Administration (2.1), Adverse Reactions (6.1), Clinical Pharmacology (12.3), Clinical Studies (14.2), (14.3)].

8.5 Geriatric Use

Clinical studies of zidovudine did not include sufficient numbers of subjects aged 65 and over to determine whether they respond differently from younger subjects. Other reported clinical experience has not identified differences in responses between the elderly and younger patients. In general, dose selection for an elderly patient should be cautious, reflecting the greater frequency of decreased hepatic, renal, or cardiac function, and of concomitant disease or other drug therapy.

8.6 Renal Impairment

In patients with severely impaired renal function (CrCl<15 mL/min), dosage reduction is recommended [see Dosage and Administration (2.4), Clinical Pharmacology (12.3)].

8.7 Hepatic Impairment

Zidovudine is eliminated from the body primarily by renal excretion following metabolism in the liver (glucuronidation). Although the data are limited, zidovudine concentrations appear to be increased in patients with severely impaired hepatic function which may increase the risk of hematologic toxicity [see Dosage and Administration (2.5), Clinical Pharmacology (12.3)].

10 OVERDOSAGE

Acute overdoses of zidovudine have been reported in pediatric patients and adults. These involved exposures up to 50 grams. No specific symptoms or signs have been identified following acute overdosage with zidovudine apart from those listed as adverse events such as fatigue, headache, vomiting, and occasional reports of hematological disturbances. All patients recovered without permanent sequelae. Hemodialysis and peritoneal dialysis appear to have a negligible effect on the removal of zidovudine while elimination of its primary metabolite, 3'-azido-3'-deoxy-5'-O-β-D-glucopyranuronosylthymidine (GZDV), is enhanced.

11 DESCRIPTION

Zidovudine (formerly called azidothymidine [AZT]), a pyrimidine nucleoside analogue active against HIV-1. The chemical name of zidovudine is 3'-azido-3'-deoxythymidine; it has the following structural formula:
Zidovudine is a white to beige, odorless, crystalline solid with a molecular weight of 267.24 and a solubility of 20.1 mg/mL in water at 25°C. The molecular formula is C10H13N5O4.
Zidovudine tablets are for oral administration. Each film-coated tablet contains 300 mg of zidovudine and the inactive ingredients hypromellose, magnesium stearate, microcrystalline cellulose, polyethylene glycol, sodium starch glycolate, and titanium dioxide.

12 CLINICAL PHARMACOLOGY

12.1 Mechanism of Action

Zidovudine is an antiviral agent [see Clinical Pharmacology (12.4)].

12.3 Pharmacokinetics

Absorption and Bioavailability: In adults, following oral administration, zidovudine is rapidly absorbed and extensively distributed, with peak serum concentrations occurring within 0.5 to 1.5 hours. The extent of absorption (AUC) was equivalent when zidovudine was administered as zidovudine tablets or syrup compared with zidovudine capsules. The pharmacokinetic properties of zidovudine in fasting adult patients are summarized in Table 6.

Table 6. Zidovudine Pharmacokinetic Parameters in Fasting Adult Patients
Parameter | Mean ± SD (except where noted)
Oral bioavailability (%) | 64 ± 10 (n = 5)
Apparent volume of distribution (L/kg) | 1.6 ± 0.6 (n = 8)
Plasma protein binding (%) | <38
CSF: plasma ratio* | 0.6 [0.04 to 2.62] (n = 39)
Systemic clearance (L/hr/kg) | 1.6 ± 0.6 (n = 6)
Renal clearance (L/hr/kg) | 0.34 ± 0.05 (n = 9)
Elimination half-life (hr)† | 0.5 to 3 (n = 19)
* Median [range].
†Approximate range.

Distribution: The apparent volume of distribution of zidovudine, following oral administration, is 1.6 ± 0.6 L/kg; and binding to plasma protein is low, <38% (Table 6).
Metabolism and Elimination: Zidovudine is primarily eliminated by hepatic metabolism. The major metabolite of zidovudine is GZDV. GZDV AUC is about 3-fold greater than the zidovudine AUC. Urinary recovery of zidovudine and GZDV accounts for 14% and 74%, respectively, of the dose following oral administration. A second metabolite, 3'-amino-3'-deoxythymidine (AMT), has been identified in the plasma following single-dose intravenous (IV) administration of zidovudine. The AMT AUC was one fifth of the zidovudine AUC. Pharmacokinetics of zidovudine were dose independent at oral dosing regimens ranging from 2 mg/kg every 8 hours to 10 mg/kg every 4 hours.
Effect of Food on Absorption: Zidovudine may be administered with or without food. The extent of zidovudine absorption (AUC) was similar when a single dose of zidovudine was administered with food.
Special Populations: Renal Impairment: Zidovudine clearance was decreased resulting in increased zidovudine and GZDV half-life and AUC in patients with impaired renal function (n = 14) following a single 200 mg oral dose (Table 7). Plasma concentrations of AMT were not determined. A dose adjustment should not be necessary for patients with creatinine clearance (CrCl) ≥15 mL/min.

Table 7. Zidovudine Pharmacokinetic Parameters in Patients With Severe Renal Impairment*
Parameter | Control Subjects (Normal Renal Function) (n = 6) | Patients With Renal Impairment (n = 14)
CrCl (mL/min) | 120 ± 8 | 18 ± 2
Zidovudine AUC (ng•hr/mL) | 1,400 ± 200 | 3,100 ± 300
Zidovudine half-life (hr) | 1 ± 0.2 | 1.4 ± 0.1
*Data are expressed as mean ± standard deviation.

Hemodialysis and Peritoneal Dialysis: The pharmacokinetics and tolerance of zidovudine were evaluated in a multiple-dose study in patients undergoing hemodialysis (n = 5) or peritoneal dialysis (n = 6) receiving escalating doses up to 200 mg 5 times daily for 8 weeks. Daily doses of 500 mg or less were well tolerated despite significantly elevated GZDV plasma concentrations. Apparent zidovudine oral clearance was approximately 50% of that reported in patients with normal renal function. Hemodialysis and peritoneal dialysis appeared to have a negligible effect on the removal of zidovudine, whereas GZDV elimination was enhanced. A dosage adjustment is recommended for patients undergoing hemodialysis or peritoneal dialysis [see Dosage and Administration (2.4)].
Hepatic Impairment: Data describing the effect of hepatic impairment on the pharmacokinetics of zidovudine are limited. However, because zidovudine is eliminated primarily by hepatic metabolism, it is expected that zidovudine clearance would be decreased and plasma concentrations would be increased following administration of the recommended adult doses to patients with hepatic impairment [see Dosage and Administration (2.5)].
Pediatric Patients: Zidovudine pharmacokinetics have been evaluated in HIV-1-infected pediatric patients (Table 8).
Patients 3 Months to 12 Years of Age: Overall, zidovudine pharmacokinetics in pediatric patients greater than 3 months of age are similar to those in adult patients. Proportional increases in plasma zidovudine concentrations were observed following administration of oral solution from 90 to 240 mg/m^2 every 6 hours. Oral bioavailability, terminal half-life, and oral clearance were comparable to adult values. As in adult patients, the major route of elimination was by metabolism to GZDV. After intravenous dosing, about 29% of the dose was excreted in the urine unchanged, and about 45% of the dose was excreted as GZDV [see Dosage and Administration (2.1)].
Patients <3 Months of Age: Zidovudine pharmacokinetics have been evaluated in pediatric patients from birth to 3 months of life. Zidovudine elimination was determined immediately following birth in 8 neonates who were exposed to zidovudine in utero. The half-life was 13 ± 5.8 hours. In neonates ≤14 days old, bioavailability was greater, total body clearance was slower, and half-life was longer than in pediatric patients >14 days old. For dose recommendations for neonates [see Dosage and Administration (2.2)].

Table 8. Zidovudine Pharmacokinetic Parameters in Pediatric Patients*
Parameter | Birth to 14 Days of Age | 14 Days to 3 Months of Age | 3 Months to 12 Years of Age
Oral bioavailability (%) | 89 ± 19 (n = 15) | 61 ± 19 (n = 17) | 65 ± 24 (n = 18)
CSF:plasma ratio | no data | no data | 0.68 [0.03 to 3.25]† (n = 38)
CL (L/hr/kg) | 0.65 ± 0.29 (n = 18) | 1.14 ± 0.24 (n = 16) | 1.85 ± 0.47 (n = 20)
Elimination half-life (hr) | 3.1 ± 1.2 (n = 21) | 1.9 ± 0.7 (n = 18) | 1.5 ± 0.7 (n = 21)
*Data presented as mean ± standard deviation except where noted.
†Median [range].

Pregnancy: Zidovudine pharmacokinetics have been studied in a Phase I study of 8 women during the last trimester of pregnancy. Zidovudine pharmacokinetics were similar to those of nonpregnant adults. Consistent with passive transmission of the drug across the placenta, zidovudine concentrations in neonatal plasma at birth were essentially equal to those in maternal plasma at delivery [see Use in Specific Populations (8.1)].
Although data are limited, methadone maintenance therapy in 5 pregnant women did not appear to alter zidovudine pharmacokinetics.
Nursing Mothers: The Centers for Disease Control and Prevention recommend that HIV-1-infected mothers not breastfeed their infants to avoid risking postnatal transmission of HIV-1. After administration of a single dose of 200 mg zidovudine to 13 HIV-1-infected women, the mean concentration of zidovudine was similar in human milk and serum [see Use In Specific Populations (8.3)].
Geriatric Patients: Zidovudine pharmacokinetics have not been studied in patients over 65 years of age.
Gender: A pharmacokinetic study in healthy male (n = 12) and female (n = 12) subjects showed no differences in zidovudine exposure (AUC) when a single dose of zidovudine was administered as the 300 mg zidovudine tablet.
Drug Interactions: [See Drug Interactions (7)].

Table 9. Effect of Coadministered Drugs on Zidovudine AUC*
Note: ROUTINE DOSE MODIFICATION OF ZIDOVUDINE IS NOT WARRANTED WITH
COADMINISTRATION OF THE FOLLOWING DRUGS.
Coadministered Drug and Dose | Zidovudine Dose | n | Zidovudine Concentrations |  | Concentration of Coadministered Drug
Coadministered Drug and Dose | Zidovudine Dose | n | AUC | Variability | Concentration of Coadministered Drug
Atovaquone 750 mg q 12 hr with food | 200 mg q 8 hr | 14 | ↑AUC 31% | Range 23% to 78%† | ↔
Fluconazole 400 mg daily | 200 mg q 8 hr | 12 | ↑AUC 74% | 95% CI: 54% to 98% | Not Reported
Lamivudine 300 mg q 12 hr | single 200 mg | 12 | ↑AUC 13% | 90% CI: 2% to 27% | ↔
Methadone 30 to 90 mg daily | 200 mg q 4 hr | 9 | ↑AUC 43% | Range 16% to 64%† | ↔
Nelfinavir 750 mg q 8 hr x 7 to 10 days | single 200 mg | 11 | ↓AUC 35% | Range 28% to 41% | ↔
Probenecid 500 mg q 6 hr x 2 days | 2 mg/kg q 8 hr x 3 days | 3 | ↑AUC 106% | Range 100% to 170%† | Not Assessed
Rifampin 600 mg daily x 14 days | 200 mg q 8 hr x 14 days | 8 | ↓AUC 47% | 90% CI: 41% to 53% | Not Assessed
Ritonavir 300 mg q 6 hr x 4 days | 200 mg q 8 hr x 4 days | 9 | ↓AUC 25% | 95% CI: 15% to 34% | ↔
Valproic acid 250 mg or 500 mg q 8 hr x 4 days | 100 mg q 8 hr x 4 days | 6 | ↑AUC 80% | Range 64% to 130%† | Not Assessed
↑ = Increase; ↓ = Decrease; ↔ = no significant change; AUC = area under the concentration versus time curve;
CI = confidence interval.
* This table is not all inclusive.
† Estimated range of percent difference.

Phenytoin: Phenytoin plasma levels have been reported to be low in some patients receiving zidovudine, while in one case a high level was documented. However, in a pharmacokinetic interaction study in which 12 HIV-1-positive volunteers received a single 300 mg phenytoin dose alone and during steady-state zidovudine conditions (200 mg every 4 hours), no change in phenytoin kinetics was observed. Although not designed to optimally assess the effect of phenytoin on zidovudine kinetics, a 30% decrease in oral zidovudine clearance was observed with phenytoin.
Ribavirin: In vitro data indicate ribavirin reduces phosphorylation of lamivudine, stavudine, and zidovudine. However, no pharmacokinetic (e.g., plasma concentrations or intracellular triphosphorylated active metabolite concentrations) or pharmacodynamic (e.g., loss of HIV-1/HCV virologic suppression) interaction was observed when ribavirin and lamivudine (n = 18), stavudine (n = 10), or zidovudine (n = 6) were coadministered as part of a multi-drug regimen to HIV-1/HCV co-infected patients [see Warnings and Precautions (5.4)].

12.4 Microbiology

Mechanism of Action: Zidovudine is a synthetic nucleoside analogue. Intracellularly, zidovudine is phosphorylated to its active 5'-triphosphate metabolite, zidovudine triphosphate (ZDV-TP). The principal mode of action of ZDV-TP is inhibition of reverse transcriptase (RT) via DNA chain termination after incorporation of the nucleotide analogue. ZDV-TP is a weak inhibitor of the cellular DNA polymerases α and γ and has been reported to be incorporated into the DNA of cells in culture.
Antiviral Activity: The antiviral activity of zidovudine against HIV-1 was assessed in a number of cell lines (including monocytes and fresh human peripheral blood lymphocytes). The EC50 and EC90 values for zidovudine were 0.01 to 0.49 µM (1 µM = 0.27 mcg/mL) and 0.1 to 9 µM, respectively. HIV-1 from therapy-naive subjects with no mutations associated with resistance gave median EC50 values of 0.011 µM (range: 0.005 to 0.11 µM) from Virco (n = 92 baseline samples from COLA40263) and 0.0017 µM (0.006 to 0.034 µM) from Monogram Biosciences (n = 135 baseline samples from ESS30009). The EC50 values of zidovudine against different HIV-1 clades (A-G) ranged from 0.00018 to 0.02 µM, and against HIV-2 isolates from 0.00049 to 0.004 µM. In cell culture drug combination studies, zidovudine demonstrates synergistic activity with the nucleoside reverse transcriptase inhibitors abacavir, didanosine, and lamivudine; the non-nucleoside reverse transcriptase inhibitors delavirdine and nevirapine; and the protease inhibitors indinavir, nelfinavir, ritonavir, and saquinavir; and additive activity with interferon alfa. Ribavirin has been found to inhibit the phosphorylation of zidovudine in cell culture.
Resistance: Genotypic analyses of the isolates selected in cell culture and recovered from zidovudine-treated patients showed mutations in the HIV-1 RT gene resulting in 6 amino acid substitutions (M41L, D67N, K70R, L210W, T215Y or F, and K219Q) that confer zidovudine resistance. In general, higher levels of resistance were associated with greater number of amino acid substitutions. In some patients harboring zidovudine-resistant virus at baseline, phenotypic sensitivity to zidovudine was restored by 12 weeks of treatment with lamivudine and zidovudine. Combination therapy with lamivudine plus zidovudine delayed the emergence of substitutions conferring resistance to zidovudine.
Cross-Resistance: In a study of 167 HIV-1-infected patients, isolates (n = 2) with multi-drug resistance to didanosine, lamivudine, stavudine, zalcitabine, and zidovudine were recovered from patients treated for ≥1 year with zidovudine plus didanosine or zidovudine plus zalcitabine. The pattern of resistance-associated amino acid substitutions with such combination therapies was different (A62V, V75I, F77L, F116Y, Q151M) from the pattern with zidovudine monotherapy, with the Q151M substitution being most commonly associated with multi-drug resistance. The substitution at codon 151 in combination with substitutions at 62, 75, 77, and 116 results in a virus with reduced susceptibility to didanosine, lamivudine, stavudine, zalcitabine, and zidovudine. Thymidine analogue mutations (TAMs) are selected by zidovudine and confer cross-resistance to abacavir, didanosine, stavudine, tenofovir, and zalcitabine.

13 NONCLINICAL TOXICOLOGY

13.1 Carcinogenesis, Mutagenesis, Impairment Of Fertility

Zidovudine was administered orally at 3 dosage levels to separate groups of mice and rats (60 females and 60 males in each group). Initial single daily doses were 30, 60, and 120 mg/kg/day in mice and 80, 220, and 600 mg/kg/day in rats. The doses in mice were reduced to 20, 30, and 40 mg/kg/day after day 90 because of treatment-related anemia, whereas in rats only the high dose was reduced to 450 mg/kg/day on day 91 and then to 300 mg/kg/day on day 279.
In mice, 7 late-appearing (after 19 months) vaginal neoplasms (5 nonmetastasizing squamous cell carcinomas, 1 squamous cell papilloma, and 1 squamous polyp) occurred in animals given the highest dose. One late-appearing squamous cell papilloma occurred in the vagina of a middle-dose animal. No vaginal tumors were found at the lowest dose.
In rats, 2 late-appearing (after 20 months), nonmetastasizing vaginal squamous cell carcinomas occurred in animals given the highest dose. No vaginal tumors occurred at the low or middle dose in rats. No other drug-related tumors were observed in either sex of either species.
At doses that produced tumors in mice and rats, the estimated drug exposure (as measured by AUC) was approximately 3 times (mouse) and 24 times (rat) the estimated human exposure at the recommended therapeutic dose of 100 mg every 4 hours.
It is not known how predictive the results of rodent carcinogenicity studies may be for humans.
Zidovudine was mutagenic in a 5178Y/TK+/- mouse lymphoma assay, positive in an in vitro cell transformation assay, clastogenic in a cytogenetic assay using cultured human lymphocytes, and positive in mouse and rat micronucleus tests after repeated doses. It was negative in a cytogenetic study in rats given a single dose.
Zidovudine, administered to male and female rats at doses up to 7 times the usual adult dose based on body surface area, had no effect on fertility judged by conception rates.
Two transplacental carcinogenicity studies were conducted in mice. One study administered zidovudine at doses of 20 mg/kg/day or 40 mg/kg/day from gestation day 10 through parturition and lactation with dosing continuing in offspring for 24 months postnatally. The doses of zidovudine administered in this study produced zidovudine exposures approximately 3 times the estimated human exposure at recommended doses. After 24 months, an increase in incidence of vaginal tumors was noted with no increase in tumors in the liver or lung or any other organ in either gender. These findings are consistent with results of the standard oral carcinogenicity study in mice, as described earlier. A second study administered zidovudine at maximum tolerated doses of 12.5 mg/day or 25 mg/day (~1,000 mg/kg nonpregnant body weight or ~450 mg/kg of term body weight) to pregnant mice from days 12 through 18 of gestation. There was an increase in the number of tumors in the lung, liver, and female reproductive tracts in the offspring of mice receiving the higher dose level of zidovudine.

13.2 Reproductive and Developmental Toxicology Studies

Oral teratology studies in the rat and in the rabbit at doses up to 500 mg/kg/day revealed no evidence of teratogenicity with zidovudine. Zidovudine treatment resulted in embryo/fetal toxicity as evidenced by an increase in the incidence of fetal resorptions in rats given 150 or 450 mg/kg/day and rabbits given 500 mg/kg/day. The doses used in the teratology studies resulted in peak zidovudine plasma concentrations (after one half of the daily dose) in rats 66 to 226 times, and in rabbits 12 to 87 times, mean steady-state peak human plasma concentrations (after one sixth of the daily dose) achieved with the recommended daily dose (100 mg every 4 hours). In an in vitro experiment with fertilized mouse oocytes, zidovudine exposure resulted in a dose-dependent reduction in blastocyst formation. In an additional teratology study in rats, a dose of 3,000 mg/kg/day (very near the oral median lethal dose in rats of 3,683 mg/kg) caused marked maternal toxicity and an increase in the incidence of fetal malformations. This dose resulted in peak zidovudine plasma concentrations 350 times peak human plasma concentrations. (Estimated area under the curve [AUC] in rats at this dose level was 300 times the daily AUC in humans given 600 mg/day.) No evidence of teratogenicity was seen in this experiment at doses of 600 mg/kg/day or less.

14 CLINICAL STUDIES

Therapy with zidovudine has been shown to prolong survival and decrease the incidence of opportunistic infections in patients with advanced HIV-1 disease and to delay disease progression in asymptomatic HIV-1-infected patients.

14.1 Adults

Combination Therapy: Zidovudine in combination with other antiretroviral agents has been shown to be superior to monotherapy for one or more of the following endpoints: delaying death, delaying development of AIDS, increasing CD4+ cell counts, and decreasing plasma HIV-1 RNA.
The clinical efficacy of a combination regimen that includes zidovudine was demonstrated in study ACTG320. This study was a multi-center, randomized, double-blind, placebo-controlled trial that compared zidovudine 600 mg/day plus EPIVIR® 300 mg/day to zidovudine plus EPIVIR plus indinavir 800 mg t.i.d. The incidence of AIDS-defining events or death was lower in the triple-drug–containing arm compared with the 2-drug–containing arm (6.1% versus 10.9%, respectively).
Monotherapy: In controlled studies of treatment-naive patients conducted between 1986 and 1989, monotherapy with zidovudine, as compared with placebo, reduced the risk of HIV-1 disease progression, as assessed using endpoints that included the occurrence of HIV-1-related illnesses, AIDS-defining events, or death. These studies enrolled patients with advanced disease (BW002), and asymptomatic or mildly symptomatic disease in patients with CD4+ cell counts between 200 and 500 cells/mm^3 (ACTG016 and ACTG019). A survival benefit for monotherapy with zidovudine was not demonstrated in the latter 2 studies. Subsequent studies showed that the clinical benefit of monotherapy with zidovudine was time limited.

14.2 Pediatric Patients

ACTG300 was a multi-center, randomized, double-blind study that provided for comparison of EPIVIR plus zidovudine to didanosine monotherapy. A total of 471 symptomatic, HIV-1-infected therapy-naive pediatric patients were enrolled in these 2 treatment arms. The median age was 2.7 years (range 6 weeks to 14 years), the mean baseline CD4+ cell count was 868 cells/mm^3, and the mean baseline plasma HIV-1 RNA was 5 log10 copies/mL. The median duration that patients remained on study was approximately 10 months. Results are summarized in Table 10.

Table 10. Number of Patients (%) Reaching a Primary Clinical Endpoint (Disease Progression or Death)
Endpoint | EPIVIR plus Zidovudine (n = 236) | Didanosine (n = 235)
HIV disease progression or death (total) Physical growth failure Central nervous system deterioration CDC Clinical Category C Death | 15 (6.4%) 7 (3%) 4 (1.7%) 2 (0.8%) 2 (0.8%) | 37 (15.7%) 6 (2.6%) 12 (5.1%) 8 (3.4%) 11 (4.7%)

14.3 Prevention of Maternal-Fetal HIV-1 Transmission

The utility of zidovudine for the prevention of maternal-fetal HIV-1 transmission was demonstrated in a randomized, double-blind, placebo-controlled trial (ACTG076) conducted in HIV-1-infected pregnant women with CD4+ cell counts of 200 to 1,818 cells/mm^3 (median in the treated group: 560 cells/mm^3) who had little or no previous exposure to zidovudine. Oral zidovudine was initiated between 14 and 34 weeks of gestation (median 11 weeks of therapy) followed by IV administration of zidovudine during labor and delivery. Following birth, neonates received oral zidovudine syrup for 6 weeks. The study showed a statistically significant difference in the incidence of HIV-1 infection in the neonates (based on viral culture from peripheral blood) between the group receiving zidovudine and the group receiving placebo. Of 363 neonates evaluated in the study, the estimated risk of HIV-1 infection was 7.8% in the group receiving zidovudine and 24.9% in the placebo group, a relative reduction intransmission risk of 68.7%. Zidovudine was well tolerated by mothers and infants. There was no difference in pregnancy-related adverse events between the treatment groups.

16 HOW SUPPLIED/STORAGE AND HANDLING

Zidovudine Tablets USP, 300 mg are white colored, biconvex, round, film-coated tablets debossed with ‘D’ on one side and ‘11’ on other side

They are supplied by State of Florida DOH Central Pharmacy as follows:

NDC | Strength | Quantity/Form | Color | Source Prod. Code
53808-0812- | 300 mg | 30 Tablets in a Blister Pack | white | 65862-024

Store at 20° to 25°C (68° to 77°F) [see USP Controlled Room Temperature].

17 PATIENT COUNSELING INFORMATION

17.1 Information About Therapy With Zidovudine

Neutropenia and Anemia: The major toxicities of zidovudine are neutropenia and/or anemia. The frequency and severity of these toxicities are greater in patients with more advanced disease and in those who initiate therapy later in the course of their infection. They should be told that if toxicity develops, they may require transfusions or drug discontinuation. They should be told of the extreme importance of having their blood counts followed closely while on therapy, especially for patients with advanced symptomatic HIV-1 disease [see Boxed Warning, Warnings and Precautions (5.1)].
Common Adverse Reactions: Other adverse effects of zidovudine include nausea and vomiting. Patients should also be encouraged to contact their physician if they experience muscle weakness, shortness of breath, symptoms of hepatitis or pancreatitis, or any other unexpected adverse events while being treated with zidovudine [see Adverse Reactions (6)].
Drug Interactions: Patients should be cautioned about the use of other medications, including ganciclovir, interferon alfa, and ribavirin, which may exacerbate the toxicity of zidovudine.
Redistribution/Accumulation of Body Fat: Redistribution or accumulation of body fat may occur in patients receiving antiretroviral therapy and that the cause and long-term health effects of these conditions are not known at this time [see Warnings and Precautions (5.6)].
Pregnancy: Pregnant women considering the use of zidovudine during pregnancy for prevention of HIV-1 transmission to their infants should be advised that transmission may still occur in some cases despite therapy. The long-term consequences of in utero and infant exposure to zidovudine are unknown, including the possible risk of cancer.
HIV-1-infected pregnant women should be advised not to breastfeed to avoid postnatal transmission of HIV to a child who may not yet be infected.
Information About Therapy With Zidovudine: Zidovudine is not a cure for HIV-1 infection, and patients may continue to acquire illnesses associated with HIV-1 infection, including opportunistic infections. Therefore, patients should be advised to seek medical care for any significant change in their health status.
Patients should be told of the importance of taking zidovudine exactly as prescribed. They should be told not to share medication and not to exceed the recommended dose. Patients should be told that the long-term effects of zidovudine are unknown at this time.
Therapy with zidovudine has not been shown to reduce the risk of transmission of HIV-1 to others through sexual contact or blood contamination.
COMBIVIR, EPIVIR, and TRIZIVIR are registered trademarks of GlaxoSmithKline.
Manufactured for:
Aurobindo Pharma USA, Inc.
2400 Route 130 North
Dayton, NJ 08810
Manufactured by:
Aurobindo Pharma Limited
Hyderabad-500 072, India

This Product was Repackaged By:

State of Florida DOH Central Pharmacy
104-2 Hamilton Park Drive
Tallahassee, FL 32304
United States